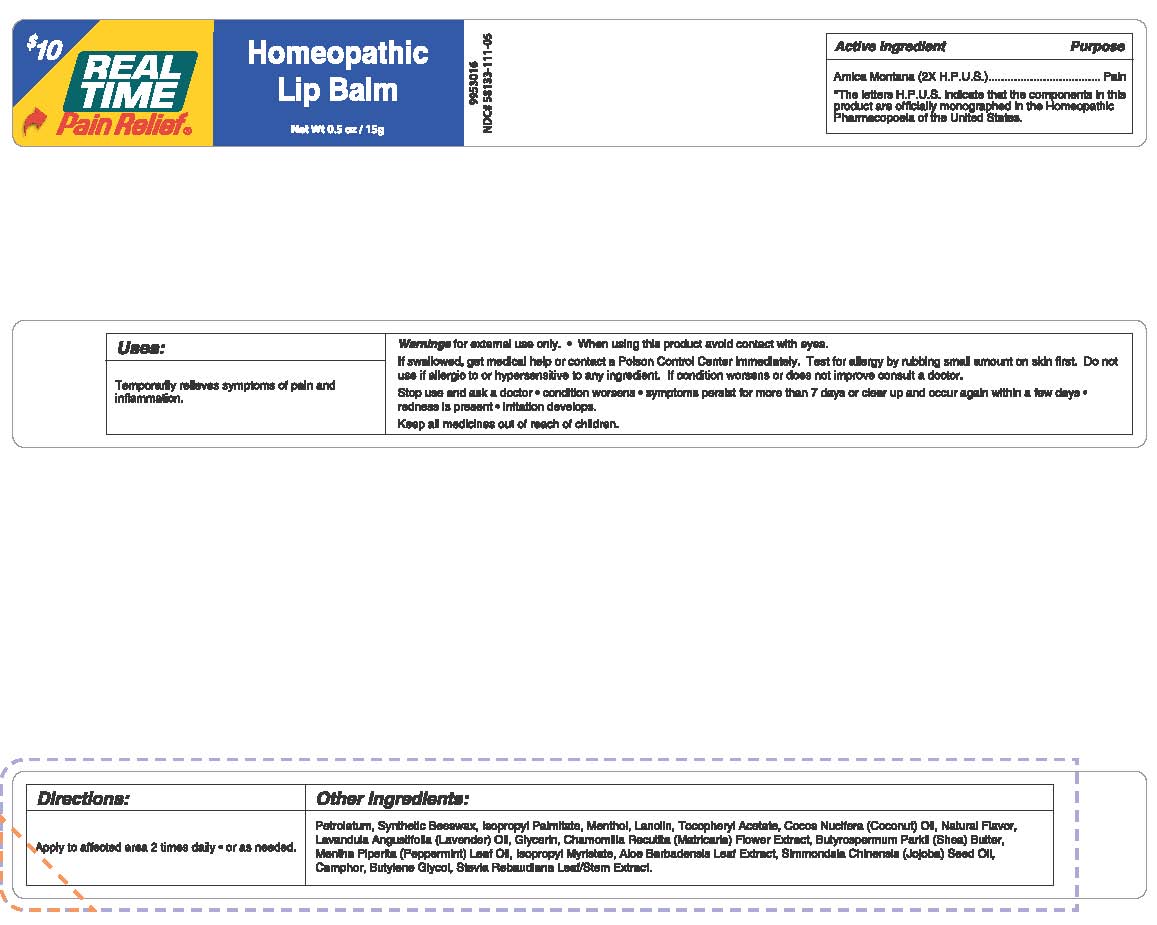 DRUG LABEL: Homeopathic Lip Balm
NDC: 58133-111 | Form: OINTMENT
Manufacturer: Cosmetic Specialty Labs, Inc.
Category: homeopathic | Type: HUMAN OTC DRUG LABEL
Date: 20180108

ACTIVE INGREDIENTS: ARNICA MONTANA 2 [hp_X]/1 g
INACTIVE INGREDIENTS: CAMPHOR LEAF OIL; BUTYLENE GLYCOL; STEVIA REBAUDIUNA LEAF; PETROLATUM; LAVANDULA ANGUSTIFOLIA WHOLE; BUTYROSPERMOL; MENTHA PIPERITA LEAF; .ALPHA.-TOCOPHEROL ACETATE; GLYCERIN; MENTHOL; LANOLIN; ALOE VERA LEAF; SIMMONDSIA CHINENSIS LEAF; COCOS NUCIFERA WHOLE; ISOPROPYL MYRISTATE; ISOPROPYL PALMITATE; SYNTHETIC WAX (1200 MW); MATRICARIA CHAMOMILLA FLOWERING TOP OIL

Real Time Pain Relief Homeopathic Lip Balm

Active Ingredient

Arnica Montana (2X H.P.U.S.)

*The letters H.P.U.S. indicate that the components in this product are officially monographed in the Homeopathic Pharmacopoeia of the United States.

Purpose

Pain

Uses

Temporarily relieves symptoms of pain and inflammation.

Warnings

For external use only.

- If swallowed, get medical help or contact a Poison Control Center Immediately.
- Test for allergy by rubbing small amount on skin first.
- Do not use if allergic to or hypersensitive to any ingredient.
- If condition worsens or does not improve consult a doctor.

When using this product

- Avoid contact with eyes

Stop use and ask a doctor if:

- Condition worsens
- Symptoms persist for more than 7 days or clear up and occur again within a few days
- Redness is present
- Irritation develops

Keep all medicines out of reach of children.

Directions

Apply to affected area 2 times daily or as needed.

Inactive Ingredients

Petrolatum, Synthetic Beeswax, Isopropyl Palmitate, Menthol, Lanolin, Tocopheryl Acetate, Cocos Nucifera (Coconut) Oil, Natural Flavor, Lavandula Angustifolia (Lavender) Oil, Glycerin, Chamomilla Recutita (Matricaria) Flower Extract, Butyrospermum Parkii (Shea) Butter, Mentha Piperita (Peppermint) Leaf Oil, Isopropyl Myristate, Also Barbadensis Leaf Extract, Simmondsia Chinensis (Jojoba) See Oil, Camphor, Butylene Glycol, Stevia Rebaudiana Leaf/Stem Extract.